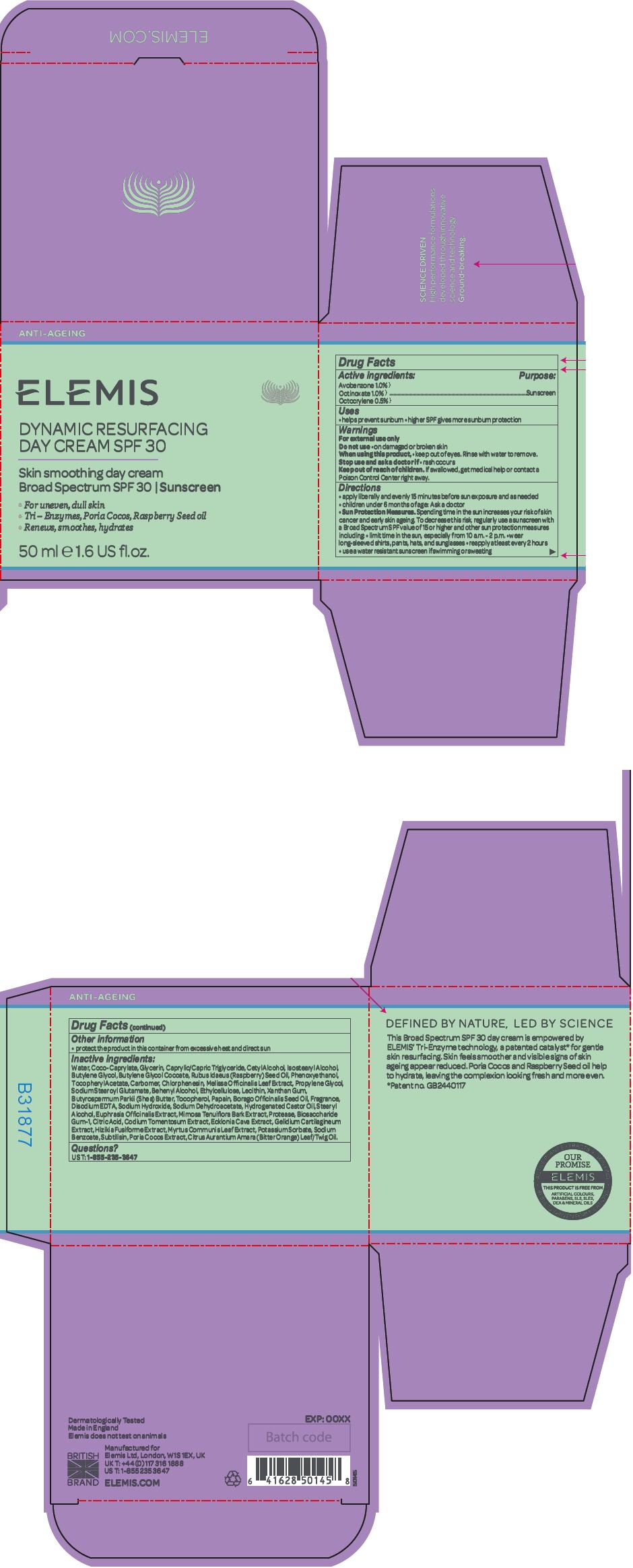 DRUG LABEL: Dynamic Resurfacing
NDC: 65912-002 | Form: CREAM
Manufacturer: ELEMIS Limited
Category: otc | Type: HUMAN OTC DRUG LABEL
Date: 20251119

ACTIVE INGREDIENTS: AVOBENZONE 10 mg/1 g; OCTINOXATE 10 mg/1 g; OCTOCRYLENE 5 mg/1 g
INACTIVE INGREDIENTS: WATER; COCO-CAPRYLATE; GLYCERIN; MEDIUM-CHAIN TRIGLYCERIDES; CETYL ALCOHOL; ISOSTEARYL ALCOHOL; BUTYLENE GLYCOL; RASPBERRY SEED OIL; PHENOXYETHANOL; .ALPHA.-TOCOPHEROL ACETATE; CHLORPHENESIN; MELISSA OFFICINALIS LEAF; PROPYLENE GLYCOL; SODIUM STEAROYL GLUTAMATE; DOCOSANOL; ETHYLCELLULOSE, UNSPECIFIED; LECITHIN, SOYBEAN; XANTHAN GUM; SHEA BUTTER; TOCOPHEROL; PAPAIN; BORAGE SEED OIL; SODIUM DEHYDROACETATE; HYDROGENATED CASTOR OIL; STEARYL ALCOHOL; EUPHRASIA STRICTA; MIMOSA TENUIFLORA BARK; BIOSACCHARIDE GUM-1; CITRIC ACID MONOHYDRATE; CODIUM TOMENTOSUM; ECKLONIA CAVA; GELIDIUM CARTILAGINEUM; EDETATE DISODIUM; SODIUM HYDROXIDE; SARGASSUM FUSIFORME; MYRTUS COMMUNIS LEAF; POTASSIUM SORBATE; SODIUM BENZOATE; SUBTILISIN; FU LING; CITRUS AURANTIUM LEAFY TWIG OIL

Dynamic Resurfacing
SPF 30

Drug Facts

Active ingredients

Avobenzone 1.0% }
Octinoxate 1.0% }
Octocrylene 0.5% }

Purpose

Sunscreen

Uses

- helps prevent sunburn
- higher SPF gives more sunburn protection

Warnings

For external use only

Do not use

- on damaged or broken skin

When using this product,

- keep out of eyes. Rinse with water to remove.

Stop use and ask a doctor if

- rash occurs

Keep out of reach of children. If swallowed, get medical help or contact a Poison Control Center right away.

Directions

- apply liberally and evenly 15 minutes before sun exposure and as needed
- children under 6 months of age: Ask a doctor
- Sun Protection Measures. Spending time in the sun increases your risk of skin cancer and early skin ageing. To decrease this risk, regularly use a sunscreen with a Broad Spectrum SPF value of 15 or higher and other sun protection measures including:
  - limit time in the sun, especially from 10 a.m. - 2 p.m.
  - wear long-sleeved shirts, pants, hats, and sunglasses
  - reapply at least every 2 hours
  - use a water resistant sunscreen if swimming or sweating

Other information

- protect the product in this container from excessive heat and direct sun

Inactive ingredients

Water, Coco-Caprylate, Glycerin, Caprylic/Capric Triglyceride, Cetyl Alcohol, Isostearyl Alcohol, Butylene Glycol, Butylene Glycol Cocoate, Rubus Idaeus (Raspberry) Seed Oil, Phenoxyethanol, Tocopheryl Acetate, Carbomer, Chlorphenesin, Melissa Officinalis Leaf Extract, Propylene Glycol, Sodium Stearoyl Glutamate, Behenyl Alcohol, Ethylcellulose, Lecithin, Xanthan Gum, Butyrospermum Parkii (Shea) Butter, Tocopherol, Papain, Borago Officinalis Seed Oil, Fragrance, Disodium EDTA, Sodium Hydroxide, Sodium Dehydroacetate, Hydrogenated Castor Oil, Stearyl Alcohol, Euphrasia Officinalis Extract, Mimosa Tenuiflora Bark Extract, Protease, Biosaccharide Gum-1, Citric Acid, Codium Tomentosum Extract, Ecklonia Cava Extract, Gelidium Cartilagineum Extract, Hizikia Fusiforme Extract, Myrtus Communis Leaf Extract, Potassium Sorbate, Sodium Benzoate, Subtilisin, Poria Cocos Extract, Citrus Aurantium Amara (Bitter Orange) Leaf/Twig Oil.

Questions?

US T: 1-855-235-3647

PRINCIPAL DISPLAY PANEL - 50 ml Jar Carton

ANTI-AGEING

ELEMIS

DYNAMIC RESURFACING
DAY CREAM SPF 30

Skin smoothing day cream
Broad Spectrum SPF 30 | Sunscreen

- For uneven, dull skin
- Tri – Enzymes, Poria Cocos, Raspberry Seed oil
- Renews, smoothes, hydrates

50 ml e 1.6 US fl.oz.